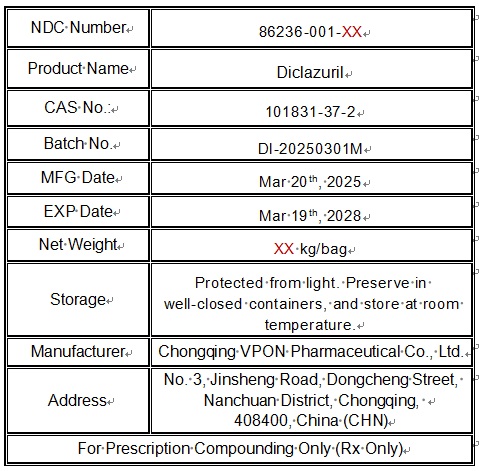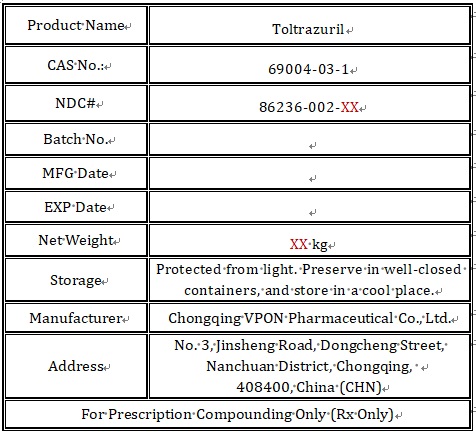 DRUG LABEL: DICLAZURIL
NDC: 86236-001 | Form: POWDER
Manufacturer: Chongqing VPON Pharmaceutical Co., Ltd.
Category: other | Type: BULK INGREDIENT - ANIMAL DRUG
Date: 20250625

ACTIVE INGREDIENTS: DICLAZURIL 1 kg/1 kg

86236-(001-002)